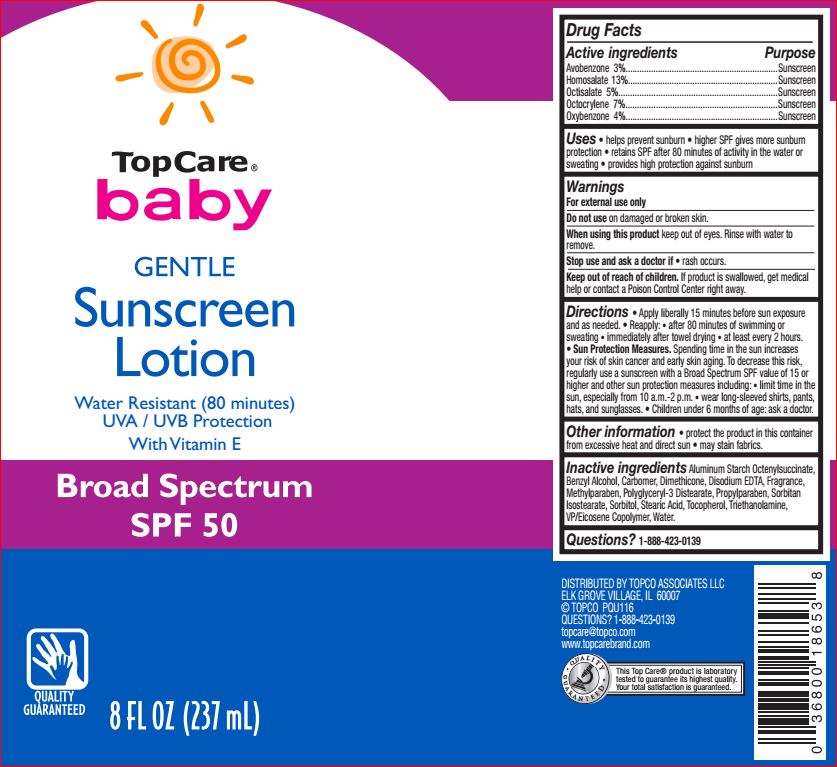 DRUG LABEL: Baby Gentle Sunscreen SPF 50
NDC: 36800-870 | Form: LOTION
Manufacturer: TopCo
Category: otc | Type: HUMAN OTC DRUG LABEL
Date: 20180615

ACTIVE INGREDIENTS: Avobenzone 3 g/100 mL; Homosalate 13 g/100 mL; Octisalate 5 g/100 mL; Octocrylene 7 g/100 mL; Oxybenzone 4 g/100 mL
INACTIVE INGREDIENTS: Aluminum Starch Octenylsuccinate; Benzyl Alcohol; CARBOMER HOMOPOLYMER TYPE B (ALLYL SUCROSE CROSSLINKED); Dimethicone; EDETATE DISODIUM; Methylparaben; Polyglyceryl-3 Distearate; Propylparaben; Sorbitan Isostearate; Sorbitol; Stearic Acid; Tocopherol; TROLAMINE; VINYLPYRROLIDONE/EICOSENE COPOLYMER; Water

Drug Facts

Active ingredients Purpose

Avobenzone 3.0%..........................Sunscreen
Homosalate 13.0%.........................Sunscreen
Octisalate 5.0%..............................Sunscreen
Octocrylene 7.0%...........................Sunscreen
Oxybenzone 4.0%..........................Sunscreen

INDICATIONS AND USAGE

Uses • helps prevent sunburn • higher SPF gives more
sunburn protection • retains SPF after 80 minutes of activity in
the water or sweating • provides high protection against sunburn

Warnings

For external use only
Do not use on damaged or broken skin
When using this product keep out of eyes.
Rinse with water to remove.
Stop use and ask a doctor if rash occurs
Keep out of reach of children. If product is swallowed, get
medical help or contact a Poison Control Center right away.

Directions

• apply liberally 15 minutes before sun exposure
• reapply: • after 80 minutes of swimming or sweating
• immediately after towel drying • at least every 2 hours
• Sun Protection Measures. Spending time in the sun increases
your risk of skin cancer and early skin aging. To decrease this
risk, regularly use a sunscreen with a broad spectrum SPF of
15 or higher and other sun protection measures including:
• limit time in the sun, especially from 10 a.m. – 2 p.m.
• wear long-sleeve shirts, pants, hats, and sunglasses
• children under 6 months: Ask a doctor

Other information • protect the product in this
container from excessive heat and direct sun • may stain fabrics

Inactive ingredients \

Aluminum Starch
Octenylsuccinate, Benzyl Alcohol, Carbomer, Dimethicone,
Disodium EDTA, Fragrance, Methylparaben, Polyglyceryl-3
Distearate, Propylparaben, Sorbitan Isostearate, Sorbitol, Stearic
Acid, Tocopherol, Triethanolamine, VP/Eicosene Copolymer, Water